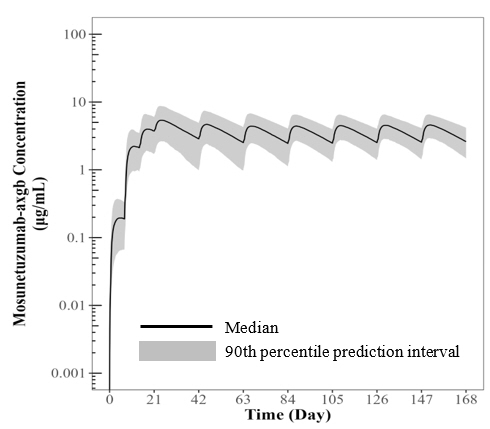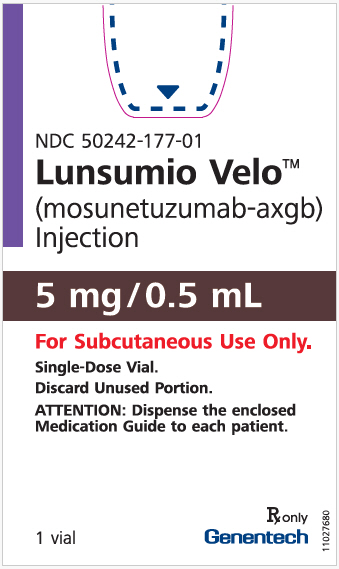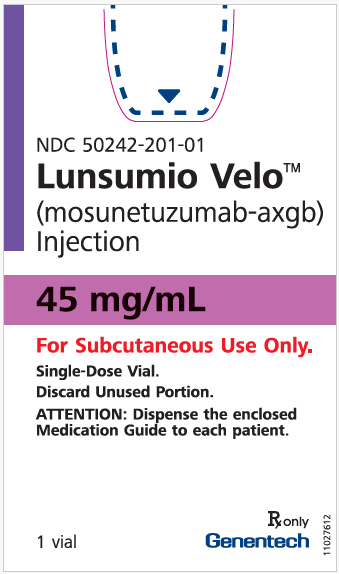 DRUG LABEL: Lunsumio Velo
NDC: 50242-177 | Form: INJECTION
Manufacturer: Genentech, Inc.
Category: prescription | Type: HUMAN PRESCRIPTION DRUG LABEL
Date: 20251219

ACTIVE INGREDIENTS: MOSUNETUZUMAB 5 mg/0.5 mL
INACTIVE INGREDIENTS: HISTIDINE 0.8 mg/0.5 mL; ACETIC ACID 0.2 mg/0.5 mL; SUCROSE 41 mg/0.5 mL; POLYSORBATE 20 0.3 mg/0.5 mL; METHIONINE 0.7 mg/0.5 mL; WATER

HIGHLIGHTS OF PRESCRIBING INFORMATION

These highlights do not include all the information needed to use LUNSUMIO VELO safely and effectively. See full prescribing information for LUNSUMIO VELO.
LUNSUMIO VELO™ (mosunetuzumab-axgb) injection, for subcutaneous use
Initial U.S. Approval: 2022

WARNING: CYTOKINE RELEASE SYNDROME

See full prescribing information for complete boxed warning.

Cytokine release syndrome (CRS), including serious or life-threatening reactions, can occur in patients receiving LUNSUMIO VELO. Initiate treatment with the LUNSUMIO VELO step-up dosing schedule to reduce the risk of CRS. Withhold LUNSUMIO VELO until CRS resolves or permanently discontinue based on severity. (2.1, 2.4, 5.1)

1 INDICATIONS AND USAGE

LUNSUMIO VELO is a bispecific CD20-directed CD3 T-cell engager indicated for the treatment of adult patients with relapsed or refractory follicular lymphoma after two or more lines of systemic therapy.

This indication is approved under accelerated approval based on response rate. Continued approval for this indication may be contingent upon verification and description of clinical benefit in a confirmatory trial(s). (1.1)

2 DOSAGE AND ADMINISTRATION

- LUNSUMIO VELO and LUNSUMIO have different dosage and route of administration instructions. Administer LUNSUMIO VELO only as a subcutaneous injection. (2.1)
- Premedicate to reduce risk of CRS. (2.3, 5.1)
- Recommended dosage for LUNSUMIO VELO for subcutaneous injection (2.2):

Day of Treatment [Cycle length = 21 days] |  | Subcutaneous Dose of LUNSUMIO VELO
Cycle 1 | Day 1 | 5 mg
Cycle 1 | Day 8 | 45 mg
Cycle 1 | Day 15 | 45 mg
Cycles 2+ | Day 1 | 45 mg

See Full Prescribing Information for instructions on preparation and administration. (2.5)

3 DOSAGE FORMS AND STRENGTHS

Injection:

- 5 mg/0.5 mL solution in a single-dose vial. (3)
- 45 mg/mL solution in a single-dose vial. (3)

4 CONTRAINDICATIONS

None. (4)

5 WARNINGS AND PRECAUTIONS

- Neurologic Toxicity, including Immune Effector Cell-Associated Neurotoxicity Syndrome: Can cause serious and life-threatening neurologic toxicity, including immune effector cell-associated neurotoxicity syndrome (ICANS). Monitor patients for signs and symptoms of neurologic toxicity during treatment; withhold or permanently discontinue based on severity. (5.2)
- Infections: Can cause serious or fatal infections. Monitor patients for signs and symptoms of infection, including opportunistic infections, and treat as needed. (5.3)
- Hemophagocytic Lymphohistiocytosis: Can cause serious or fatal reactions. For suspected cases, interrupt LUNSUMIO VELO and evaluate and treat promptly. (5.4)
- Cytopenias: Monitor complete blood cell counts during treatment. (5.5)
- Tumor Flare: Can cause serious tumor flare reactions. Monitor patients at risk for complications of tumor flare. (5.6)
- Risk of Medication Errors with Incorrect Product Use: Ensure that the correct formulation is being prescribed, dispensed, and administered. (5.7)
- Embryo-Fetal Toxicity: May cause fetal harm. Advise females of reproductive potential of the potential risk to the fetus and to use effective contraception. (5.8, 8.1, 8.3)

6 ADVERSE REACTIONS

The most common adverse reactions (≥ 20%) are injection site reactions, fatigue, rash, CRS, COVID-19 infection, musculoskeletal pain, and diarrhea. The most common Grade 3 to 4 laboratory abnormalities (≥ 15%) are decreased lymphocyte count, decreased neutrophil count, and increased uric acid. (6.1)

To report SUSPECTED ADVERSE REACTIONS, contact Genentech at 1-888-835-2555 or FDA at 1-800-FDA-1088 or www.fda.gov/medwatch.

8 USE IN SPECIFIC POPULATIONS

Lactation: Advise not to breastfeed. (8.2)

FULL PRESCRIBING INFORMATION

WARNING: CYTOKINE RELEASE SYNDROME

Cytokine release syndrome (CRS), including serious or life-threatening reactions, can occur in patients receiving LUNSUMIO VELO. Initiate treatment with the LUNSUMIO VELO step-up dosing schedule to reduce the risk of CRS. Withhold LUNSUMIO VELO until CRS resolves or permanently discontinue based on severity [see Dosage and Administration (2.1 and 2.4) and Warnings and Precautions (5.1)].

1 INDICATIONS AND USAGE

1.1 Follicular Lymphoma

LUNSUMIO VELO is indicated for the treatment of adult patients with relapsed or refractory follicular lymphoma after two or more lines of systemic therapy.

This indication is approved under accelerated approval based on response rate [see Clinical Studies (14)]. Continued approval for this indication may be contingent upon verification and description of clinical benefit in a confirmatory trial(s).

2 DOSAGE AND ADMINISTRATION

2.1 Important Dosing Information

- LUNSUMIO VELO and LUNSUMIO have different dosage and administration instructions [see Dosage and Administration (2.2) and Warnings and Precautions (5.7)].
  - LUNSUMIO VELO is for subcutaneous use only.
  - Check the product label to ensure that the correct formulation (LUNSUMIO VELO or LUNSUMIO) is being prescribed and administered.
  - Do not substitute LUNSUMIO VELO for or with LUNSUMIO.
- Administer LUNSUMIO VELO to well-hydrated patients.
- Premedicate before each dose in Cycle 1 [see Dosage and Administration (2.3)].
- LUNSUMIO VELO should only be administered by a qualified healthcare professional with appropriate medical support to manage severe reactions such as CRS and neurologic toxicity, including ICANS [see Warnings and Precautions (5.1 and 5.2)].

2.2 Recommended Dosage

The recommended dosage for LUNSUMIO VELO subcutaneous injection is presented in Table 1.

Administer for 8 cycles unless patients experience unacceptable toxicity or disease progression.

For patients who achieve a complete response, no further treatment beyond 8 cycles is required. For patients who achieve a partial response or have stable disease in response to treatment with LUNSUMIO VELO after 8 cycles, an additional 9 cycles of treatment (17 cycles total) should be administered, unless a patient experiences unacceptable toxicity or disease progression.

Table 1. Recommended Dose and Schedule of LUNSUMIO VELO Subcutaneous Injection (21-Day Treatment Cycles)
Day of Treatment |  | Subcutaneous Dose of LUNSUMIO VELO
Cycle 1 | Day 1 | 5 mg
Cycle 1 | Day 8 | 45 mg
Cycle 1 | Day 15 | 45 mg
Cycles 2+ | Day 1 | 45 mg

Table 2. Recommendations for Restarting Therapy with LUNSUMIO VELO Subcutaneous Injection After Dose Delay
Last Subcutaneous Dose Administered | Time Since Last Dose Administered | Action for Next Subcutaneous Dose(s)
5 mg Cycle 1 Day 1 | 1 week to 2 weeks | Administer 45 mg (Cycle 1 Day 8) [Administer premedication as per Cycle 1.] , then resume the planned treatment schedule.
5 mg Cycle 1 Day 1 | Greater than 2 weeks | Repeat 5 mg (Cycle 1 Day 1), then administer 45 mg (Cycle 1 Day 8) and resume the planned treatment schedule.
45 mg Cycle 1 Day 8 | 1 week to less than 6 weeks | Administer 45 mg (Cycle 1 Day 15), then resume the planned treatment schedule.
45 mg Cycle 1 Day 8 | Greater than or equal to 6 weeks | Repeat 5 mg, then administer 45 mg (Cycle 1 Day 15) 7 days later and resume the planned treatment schedule.
45 mg Cycle 1 Day 15 | 1 week to less than 6 weeks | Administer 45 mg (Cycle 2 Day 1), then resume the planned treatment schedule.
45 mg Cycle 1 Day 15 | Greater than or equal to 6 weeks | Repeat 5 mg (Cycle 2 Day 1), then administer 45 mg (Cycle 2 Day 8) followed by 45 mg on Day 1 of subsequent cycles.
45 mg Cycle 2 onwards | 3 weeks to less than 6 weeks | Administer 45 mg, then resume the planned treatment schedule.
45 mg Cycle 2 onwards | Greater than or equal to 6 weeks | Repeat 5 mg on Day 1 during the next cycle, then administer 45 mg on Day 8, followed by 45 mg on Day 1 of subsequent cycles.

2.3 Recommended Premedication

Premedications to reduce the risk of CRS are outlined in Table 3 [see Warnings and Precautions (5.1)].

Table 3. Premedication to be Administered Prior to LUNSUMIO VELO Subcutaneous Injection
Treatment Cycle | Patients Requiring Premedication | Premedication | Dosage
Cycle 1 | All patients | Corticosteroid | Dexamethasone 20 mg (preferred) oral or intravenous or methylprednisolone 80 mg oral or intravenous
Cycle 1 | All patients | Antihistamine [Antihistamine and antipyretic premedications are optional in all cycles.] | Diphenhydramine hydrochloride 50 mg to 100 mg or equivalent oral or intravenous antihistamine
Cycle 1 | All patients | Antipyretic | Oral acetaminophen (500 mg to 1,000 mg)
Cycles 2+ | Patients who experienced any grade CRS with the previous dose | Corticosteroid | Dexamethasone 20 mg (preferred) oral or intravenous or methylprednisolone 80 mg oral or intravenous
Cycles 2+ | Patients who experienced any grade CRS with the previous dose | Antihistamine | Diphenhydramine hydrochloride 50 mg to 100 mg or equivalent oral or intravenous antihistamine
Cycles 2+ | Patients who experienced any grade CRS with the previous dose | Antipyretic | Oral acetaminophen (500 mg to 1,000 mg)

2.4 Dosage Modifications for Adverse Reactions

See Tables 4 and 5 for the recommended dosage modifications for adverse reactions of CRS and neurologic toxicity, including immune effector cell-associated neurotoxicity (ICANS). See Table 6 for the recommended dosage modifications for other adverse reactions following administration of LUNSUMIO VELO.

Dosage Modifications for Cytokine Release Syndrome

Identify CRS based on clinical presentation [see Warnings and Precautions (5.1)]. Evaluate for and treat other causes of fever, hypoxia, and hypotension.

If CRS is suspected, withhold LUNSUMIO VELO until CRS resolves, manage according to the recommendations in Table 4 and per current practice guidelines. Administer supportive therapy for CRS, which may include intensive care for severe or life-threatening CRS.

Table 4. Recommendations for Management of Cytokine Release Syndrome with LUNSUMIO VELO Subcutaneous Administration
Grade [Based on American Society for Transplantation and Cellular Therapy (ASTCT) 2019 grading for CRS.] | Presenting Symptoms | Actions [If CRS is refractory to management, consider other causes including hemophagocytic lymphohistiocytosis.]
Grade 1 | Fever ≥ 100.4°F (38°C) [Premedication may mask fever, therefore if clinical presentation is consistent with CRS, follow these management guidelines.] | - Ensure CRS symptoms are resolved prior to the next dose of LUNSUMIO VELO. [Refer to Table 2 for information on restarting LUNSUMIO VELO after dose delays [see Dosage and Administration (2.2)].] - Administer premedication [Refer to Table 3 for additional information on premedication.] prior to next dose of LUNSUMIO VELO and monitor patient more frequently.
Grade 2 | Fever ≥ 100.4°F (38°C) with: | - Ensure CRS symptoms are resolved for at least 72 hours prior to the next dose of LUNSUMIO VELO.
Grade 2 | Hypotension not requiring vasopressors | - Administer premedication prior to next dose of LUNSUMIO VELO.
Grade 2 | and/or | - For the next dose of LUNSUMIO VELO, monitor more frequently and consider hospitalization.
Grade 2 | hypoxia requiring low-flow oxygen [Low-flow oxygen defined as oxygen delivered at < 6 L/minute; high-flow oxygen defined as oxygen delivered at ≥ 6 L/minute.] by nasal cannula or blow-by. | Recurrent Grade 2 CRS; - Manage per Grade 3 CRS.
Grade 3 | Fever ≥ 100.4°F (38°C) with: | - Ensure CRS symptoms are resolved for at least 72 hours prior to the next dose of LUNSUMIO VELO.
Grade 3 | Hypotension requiring a vasopressor (with or without vasopressin) | - Administer premedication prior to next dose of LUNSUMIO VELO.
Grade 3 | and/or | - For the next dose of LUNSUMIO VELO, monitor more frequently and hospitalize for the next dose.
Grade 3 | hypoxia requiring high flow oxygen by nasal cannula, face mask, non-rebreather mask, or Venturi mask. | - If CRS occurred after the 5 mg or 45 mg dose, administer 5 mg as the next dose. Resume treatment schedule after recovery. If the 5 mg dose is tolerated without grade 3 CRS, resume subsequent doses at 45 mg.
Grade 3 |  | Recurrent Grade 3 CRS; - Permanently discontinue LUNSUMIO VELO. - Manage CRS per current practice guidelines and provide supportive therapy, which may include intensive care.
Grade 4 | Fever ≥ 100.4°F (38°C) with: | - Permanently discontinue LUNSUMIO VELO. - Manage CRS per current practice guidelines and provide supportive therapy, which may include intensive care.
Grade 4 | Hypotension requiring multiple vasopressors (excluding vasopressin) | - Permanently discontinue LUNSUMIO VELO. - Manage CRS per current practice guidelines and provide supportive therapy, which may include intensive care.
Grade 4 | and/or | - Permanently discontinue LUNSUMIO VELO. - Manage CRS per current practice guidelines and provide supportive therapy, which may include intensive care.
Grade 4 | hypoxia requiring oxygen by positive pressure (e.g., CPAP, BiPAP, intubation and mechanical ventilation). | - Permanently discontinue LUNSUMIO VELO. - Manage CRS per current practice guidelines and provide supportive therapy, which may include intensive care.

Dosage Modifications for Neurologic Toxicity, including ICANS

Management recommendations for neurologic toxicity, including ICANS, are summarized in Table 5. At the first sign of neurologic toxicity, including ICANS, consider neurology evaluation and withholding of LUNSUMIO VELO based on the type and severity of neurotoxicity. Rule out other causes of neurologic symptoms. Provide supportive therapy, which may include intensive care.

Table 5. Recommendations for Management of Neurologic Toxicity (including ICANS)
Adverse Reaction | Severity [Based on National Cancer Institute Common Terminology Criteria for Adverse Events (NCI CTCAE), version 4.0.] , [Based on American Society for Transplantation and Cellular Therapy (ASTCT) 2019 grading for ICANS.] | Actions
Neurologic Toxicity (including ICANS) | Grade 1 | - Continue LUNSUMIO VELO and monitor neurologic toxicity symptoms. - If ICANS, manage per current practice guidelines.
Neurologic Toxicity (including ICANS) | Grade 2 | - Withhold LUNSUMIO VELO until neurologic toxicity symptoms improve to Grade 1 or baseline for at least 72 hours. [See Table 2 for recommendations on restarting LUNSUMIO VELO after dose delays [see Dosage and Administration (2.2)].] - Provide supportive therapy, and consider neurologic evaluation. - If ICANS, manage per current practice guidelines.
Neurologic Toxicity (including ICANS) | Grade 3 | - Withhold LUNSUMIO VELO until neurologic toxicity symptoms improve to Grade 1 or baseline for at least 72 hours. - Provide supportive therapy, which may include intensive care, and consider neurology evaluation. - If ICANS, manage per current practice guidelines. - If recurrence of ICANS, permanently discontinue LUNSUMIO VELO.
Neurologic Toxicity (including ICANS) | Grade 4 | - Permanently discontinue LUNSUMIO VELO. - Provide supportive therapy, which may include intensive care, and consider neurology evaluation. - If ICANS, manage per current practice guidelines.

Other Adverse Reactions

Table 6. Recommended Dosage Modification for Other Adverse Reactions
Adverse Reactions [Based on National Cancer Institute Common Terminology Criteria for Adverse Events (NCI CTCAE), version 4.0.] | Severity | Actions
Infections [see Warnings and Precautions (5.3)] | Grades 1 – 4 | - Withhold LUNSUMIO VELO in patients with active infection until the infection resolves. [See Table 2 for recommendations on restarting LUNSUMIO VELO after dose delays [see Dosage and Administration (2.2)].] - For Grade 4, consider permanent discontinuation of LUNSUMIO VELO.
Neutropenia [see Warnings and Precautions (5.4)] | Absolute neutrophil count less than 0.5 × 10^9/L | - Withhold LUNSUMIO VELO until absolute neutrophil count is 0.5 × 10^9/L or higher.
Other Adverse Reactions [see Warnings and Precautions (5.5) and Adverse Reactions (6.1)] | Grade 3 or higher | - Withhold LUNSUMIO VELO until the toxicity resolves to Grade 1 or baseline. - Permanently discontinue LUNSUMIO VELO if a Grade 4 injection site reaction occurs.

2.5 Preparation and Administration

If the LUNSUMIO VELO dose is not administered immediately, refer to "Storage of Prepared Syringe" section below.

- To prevent medication errors, check the vial labels to ensure that the drug being prepared and administered is LUNSUMIO VELO for subcutaneous administration. A peel-off label is provided on the LUNSUMIO VELO Prescribing Information that should be attached to the final prepared syringe. Remove the peel-off label from the Prescribing Information in the LUNSUMIO VELO carton before discarding the carton. Affix the peel-off label to the prepared LUNSUMIO VELO syringe.
- Parenteral drug products should be inspected visually for particulate matter and discoloration prior to administration, whenever solution and container permit. Do not use if the solution is discolored, or cloudy, or if foreign particles are present.
- Each LUNSUMIO VELO 5 mg/0.5 mL and 45 mg/mL vial are supplied as ready-to-use solution that do not need dilution prior to subcutaneous administration. LUNSUMIO VELO vials are for one-time use in one patient only.
- No incompatibilities between LUNSUMIO VELO and polypropylene or polycarbonate syringe material, stainless-steel transfer and injection needles, and polyethylene or polypropylene syringe closing caps have been observed.

Preparation of the Syringe

- Use aseptic technique to prepare LUNSUMIO VELO.
- Select the appropriate strength vial based on the prescribed dose.
- Withdraw the required volume of LUNSUMIO VELO solution from the vial with a syringe and an appropriately sized transfer needle (18G to 21G recommended). The smallest syringe that can accurately deliver the injection volume should be used. Discard any unused portion left in the vial.
- Remove the transfer needle and attach an appropriately sized injection needle (25G to 30G recommended).
- Apply peel-off label from the Prescribing Information to the prepared drug product.
- Once transferred from the vial to the syringe, LUNSUMIO VELO solution for injection should be injected immediately because LUNSUMIO VELO solution for injection does not contain any antimicrobial-preservative.

Administration

Inject the required volume of LUNSUMIO VELO into the subcutaneous tissue of the abdomen or thigh, changing the site of injection with each dose. Do not inject into tattoos, moles, scars or areas where the skin is red, bruised, tender, hard, or not intact. The dose should be administered subcutaneously over approximately 30 seconds to 1 minute.

Storage of Prepared Syringe

- The prepared syringe should be used immediately. If not used immediately, replace the transfer needle with a syringe closing cap. Do not attach an injection needle.
- The capped syringe can be stored refrigerated at 2°C to 8°C (36°F to 46°F) for up to 32 hours protected from light and/or at 9°C to 25°C (37°F to 77°F) for up to 8 hours at ambient light.
- Once removed from refrigerated storage, the solution can be equilibrated to ambient temperature up to 25°C (77°F) prior to administration. Do not warm LUNSUMIO VELO in any other way.

3 DOSAGE FORMS AND STRENGTHS

LUNSUMIO VELO is a sterile, colorless to slightly brownish-yellow solution for subcutaneous injection available as:

- Injection: 5 mg/0.5 mL in a single-dose vial
- Injection: 45 mg/mL in a single-dose vial

4 CONTRAINDICATIONS

None.

5 WARNINGS AND PRECAUTIONS

5.1 Cytokine Release Syndrome

LUNSUMIO VELO can cause CRS, including serious or life-threatening reactions [see Adverse Reactions (6.1)].

CRS occurred in 30% of patients who received LUNSUMIO VELO at the recommended dosage in the clinical trial (N = 94), with Grade 1 CRS occurring in 20%, Grade 2 in 7%, and Grade 3 in 2.1% of patients. Among 28 patients who experienced CRS, CRS recurred in 14%. CRS occurred most commonly after the first two doses: 19% of patients experienced CRS after the Cycle 1 Day 1 dose, 13% after the Cycle 1 Day 8 dose, and 2.1% after the Cycle 1 Day 15 dose.

The median time to CRS onset from the start of LUNSUMIO VELO administration was 17 hours (range: 7 to 33 hours) with the Cycle 1 Day 1 dose, and 62 hours (range: 30 to 113 hours) with the Cycle 1 Day 8 dose. CRS resolved in all patients, after a median duration of 2 days (range: 1 to 15 days).

Clinical signs and symptoms of CRS included fever, hypotension, hypoxia, chills, tachycardia, and headache. Concurrent neurologic adverse reactions occurred in 5% of patients and included but were not limited to headache, dizziness, lethargy, memory impairment, and peripheral neuropathy.

Initiate therapy according to LUNSUMIO VELO step-up dosing schedule to reduce the risk of CRS [see Dosage and Administration (2.3)]. Administer pretreatment medications to reduce the risk of CRS, ensure adequate hydration, and monitor patients following administration of LUNSUMIO VELO accordingly.

At the first sign of CRS, immediately evaluate patients for hospitalization, manage per current practice guidelines, and administer supportive care; withhold or permanently discontinue LUNSUMIO VELO based on severity [see Dosage and Administration (2.4)].

Patients who experience CRS (or other adverse reactions that impair consciousness) should be evaluated and advised not to drive and to refrain from operating heavy or potentially dangerous machinery until resolution.

5.2 Neurologic Toxicity, including Immune Effector Cell-Associated Neurotoxicity Syndrome

LUNSUMIO VELO can cause serious and life-threatening neurologic toxicity, including immune effector cell-associated neurotoxicity syndrome (ICANS) [see Adverse Reactions (6.1)].

Neurologic toxicity occurred in 53% of patients who received LUNSUMIO VELO at the recommended dosage in the clinical trial (N = 94), with Grade 3 neurologic toxicity occurring in 1.1% of patients. The most frequent neurologic toxicities were headache (17%), insomnia (15%), dizziness (10%), and mental status changes (7%, including confusion and lethargy). ICANS or suspected ICANS was reported in 3.1% of patients (all Grade 1).

Across a broader clinical trial population, ICANS or suspected ICANS occurred in 2.2% (21/949) of patients who received LUNSUMIO or LUNSUMIO VELO. The most frequent manifestations included confusional state and lethargy. Twenty patients had Grade 1-2 reactions and 1 patient had a Grade 3 event. The majority of cases (75%) occurred during the first cycle of treatment. The median time to onset was 17 days (range: 1 to 48 days). In total, 88% of cases resolved after a median duration of 3 days (range: 1 to 20 days).

Coadministration of LUNSUMIO VELO with other products that cause dizziness or mental status changes may increase the risk of neurologic toxicity.

Monitor patients for signs and symptoms of neurologic toxicity during treatment. At the first sign of neurologic toxicity, including ICANS, immediately evaluate the patient, consider neurology evaluation as appropriate, and provide supportive therapy based on severity; withhold or permanently discontinue LUNSUMIO VELO based on severity and follow management recommendations [see Dosage and Administration (2.4)].

Patients who experience neurologic toxicity such as tremors, dizziness, insomnia, severe neurotoxicity, or any other adverse reactions that impair consciousness should be evaluated, including potential neurology evaluation, and patients at increased risk should be advised not to drive and to refrain from operating heavy or potentially dangerous machinery until resolution.

5.3 Infections

LUNSUMIO VELO can cause serious or fatal infections [see Adverse Reactions (6.1)].

Among patients who received LUNSUMIO VELO at the recommended dosage in the clinical trial, serious infections, including opportunistic infections, occurred in 17%, with Grade 3 or 4 infections in 16% and fatal infections in 3.2% of patients. The most common Grade 3 or greater infections were pneumonia, sepsis, and COVID-19.

Monitor patients for signs and symptoms of infection prior to and during treatment with LUNSUMIO VELO and treat appropriately. LUNSUMIO VELO should not be administered in the presence of active infection. Caution should be exercised when considering use in patients with a history of recurring or chronic infections (e.g., chronic, active Epstein-Barr Virus), with underlying conditions that may predispose to infections or who have had significant prior immunosuppressive treatment. Administer prophylactic antimicrobials according to guidelines.

Withhold LUNSUMIO VELO or consider permanent discontinuation based on severity [see Dosage and Administration (2.4)].

5.4 Hemophagocytic Lymphohistiocytosis

LUNSUMIO VELO can cause fatal or serious hemophagocytic lymphohistiocytosis (HLH). HLH is a potentially life-threatening, hyperinflammatory syndrome that is independent of CRS. Common manifestations include fever, elevated ferritin, hemophagocytosis, cytopenias, coagulopathy, hepatitis, and splenomegaly.

Across a broader clinical trial population, HLH occurred in 0.5% (7/1536) of patients who received LUNSUMIO or LUNSUMIO VELO. Most cases (5/7) were identified within the first 28 days following initiation of treatment, with 3 cases preceded by diagnosed or suspected CRS. Of the 7 cases of HLH, 6 had fatal outcomes, with 2 deaths from HLH alone and 4 deaths with concurrent unresolved HLH. Of the 7 cases of HLH, 4 occurred in the context of concurrent EBV and/or CMV infection.

Monitor for clinical signs and symptoms of HLH. Consider HLH when the presentation of CRS is atypical or prolonged, or when there are features of macrophage activation. For suspected HLH, interrupt LUNSUMIO VELO and evaluate and treat promptly for HLH per current practice guidelines.

5.5 Cytopenias

LUNSUMIO VELO can cause serious or severe cytopenias, including lymphopenia, neutropenia, anemia, and thrombocytopenia [see Adverse Reactions (6.1)].

Among patients who received LUNSUMIO VELO at the recommended dosage in the clinical trial (N = 94), Grade 3 or 4 decreased lymphocytes occurred in 69%, decreased neutrophils occurred in 26%, decreased hemoglobin in 10%, and decreased platelets in 6% of patients. Grade 4 decreased lymphocytes occurred in 22%, decreased neutrophils in 9% and decreased platelets in 3.2% of patients. Febrile neutropenia occurred in 2.1% of patients.

Monitor complete blood counts throughout treatment. Based on the severity of cytopenias, temporarily withhold, or permanently discontinue LUNSUMIO VELO. Consider prophylactic granulocyte colony-stimulating factor administration as applicable [see Dosage and Administration (2.4)].

5.6 Tumor Flare

LUNSUMIO VELO can cause serious or severe tumor flare [see Adverse Reactions (6.1)].

Among patients who received LUNSUMIO VELO at the recommended dosage in the clinical trial (N = 94), tumor flare occurred in 1.1% of patients. Manifestations may include new or worsening pleural effusions, localized pain and swelling at the sites of lymphoma lesions, and tumor inflammation.

Patients with bulky tumors or disease located in close proximity to airways or a vital organ should be monitored closely during initial therapy. Monitor for signs and symptoms of compression or obstruction due to mass effect secondary to tumor flare. If compression or obstruction develops, institute standard treatment of these complications.

5.7 Risk of Medication Errors with Incorrect Product Use

Mosunetuzumab-axgb is available in two formulations: as an injection for subcutaneous use (LUNSUMIO VELO) and an injection for intravenous use (LUNSUMIO). Check the product labels to ensure that the correct formulation is being prescribed, dispensed, and administered to the patient [see Dosage and Administration (2.2 and 2.5)]. Do not substitute LUNSUMIO VELO for or with LUNSUMIO.

5.8 Embryo-Fetal Toxicity

Based on its mechanism of action, LUNSUMIO VELO may cause fetal harm when administered to a pregnant woman. Advise pregnant women of the potential risk to the fetus. Advise females of reproductive potential to use effective contraception during treatment with LUNSUMIO VELO and for 3 months after the last dose [see Use in Specific Populations (8.1, 8.3)].

6 ADVERSE REACTIONS

The following adverse reactions are described elsewhere in the labeling:

- Cytokine Release Syndrome [see Warnings and Precautions (5.1)]
- Neurologic Toxicity, including Immune Effector Cell-associated Neurotoxicity Syndrome [see Warnings and Precautions (5.2)]
- Infections [see Warnings and Precautions (5.3)]
- Hemophagocytic Lymphohistiocytosis [see Warnings and Precautions (5.4)]
- Cytopenias [see Warnings and Precautions (5.5)]
- Tumor Flare [see Warnings and Precautions (5.6)]

6.1 Clinical Trials Experience

Because clinical trials are conducted under widely varying conditions, adverse reaction rates observed in the clinical trials of a drug cannot be directly compared to rates in the clinical trials of another drug and may not reflect the rates observed in practice.

Relapsed or Refractory Follicular Lymphoma

The safety of LUNSUMIO VELO was evaluated in an open-label, multicenter study which included a cohort of 94 patients with relapsed or refractory follicular lymphoma (FL) after at least two lines of systemic therapy [see Clinical Studies (14)]. Patients received step-up doses of 5 mg via subcutaneous injection on Cycle 1 Day 1 and 45 mg on Cycle 1 Day 8, followed by 45 mg on Cycle 1 Day 15, then 45 mg every 3 weeks in subsequent cycles. A treatment cycle was 21 days. The median number of cycles was 8 (range: 1 to 17), with 78% of patients exposed for at least 8 cycles and 6% exposed for 17 cycles.

The median age was 65 years (range: 35 to 84 years), 56% were male, 85% were White, 2.1% were Black or African American, 11% were Asian, and 2% were Hispanic or Latino.

Serious adverse reactions occurred in 39% of patients. Serious adverse reactions in ≥ 10% of patients included infection (17%, including pneumonia, other respiratory tract infections, and sepsis) and CRS (15%). Fatal adverse reactions occurred in 4.3% of patients from COVID-19 (3.2%) and HLH (1.1%).

Permanent discontinuation LUNSUMIO VELO due to an adverse reaction occurred in 7% of patients, including from COVID-19.

Dosage interruptions of LUNSUMIO VELO due to an adverse reaction occurred in 40% of patients. Adverse reactions which required dosage interruption in ≥ 5% of patients included COVID-19 and neutropenia.

The most common adverse reactions (≥ 20%), excluding laboratory abnormalities, were injection site reactions, fatigue, rash, CRS, COVID-19 infection, musculoskeletal pain, and diarrhea. The most common Grade 3-4 laboratory abnormalities (≥ 15%) were decreased lymphocyte count, decreased neutrophil count, and increased uric acid. Grade 4 laboratory abnormalities in > 5% included lymphocyte count decreased (22%) and neutrophil count decreased (9%).

Table 7 summarizes the adverse reactions.

Table 7. Adverse Reactions (≥ 10%) in Patients with Relapsed or Refractory FL Who Received LUNSUMIO VELO Subcutaneous Injection in GO29781
Adverse Reaction | LUNSUMIO VELO (N = 94)
Adverse Reaction | All Grades (%) | Grade 3 or 4 (%)
Immune system disorders
Cytokine release syndrome | 30 | 2.1
General disorders and administration site conditions
Injection site reactions [Injection site reactions includes injection site reaction, injection site discharge, injection site erythema, injection site edema, injection site pain, injection site pruritus and injection site rash.] | 69 | 0
Fatigue [Fatigue includes fatigue, asthenia, and lethargy.] | 39 | 0
Edema [Edema includes edema, edema peripheral, face edema, pulmonary edema, fluid overload, and related terms.] | 13 | 0
Pyrexia | 11 | 1.1
Chills | 11 | 0
Skin and subcutaneous tissue disorders
Rash [Rash includes rash, injection site rash, erythema, dermatitis, palmar-plantar erythrodysesthesia, erythema multiforme, urticaria, and related terms.] | 35 | 3.2
Dry skin | 11 | 0
Nervous system
Headache | 17 | 0
Peripheral neuropathy [Peripheral neuropathy includes peripheral neuropathy, peripheral sensory neuropathy, peripheral motor neuropathy, paresthesia, dysesthesia, hypoesthesia, burning sensation, and neuralgia.] | 11 | 0
Dizziness [Dizziness includes dizziness and vertigo.] | 10 | 0
Musculoskeletal and connective tissue disorders
Musculoskeletal pain [Musculoskeletal pain includes musculoskeletal pain, back pain, myalgia, musculoskeletal chest pain, and neck pain.] | 20 | 0
Arthralgia | 13 | 0
Respiratory, thoracic, and mediastinal disorders
Cough | 13 | 0
Dyspnea | 11 | 0
Gastrointestinal disorders
Diarrhea | 20 | 0
Nausea | 14 | 0
Constipation | 14 | 0
Abdominal pain | 13 | 0
Infections
COVID-19 [Adverse reaction with fatal outcome.] , [Grade 5 COVID-19 occurred in 3.2% of patients.] | 27 | 4.3
Upper respiratory tract infection [Upper respiratory tract infection includes upper respiratory tract infection, nasopharyngitis, sinusitis, rhinovirus infection, and related terms.] | 15 | 2.1
Pneumonia [Pneumonia includes lung consolidation and specific types of pneumonia including COVID-19 pneumonia.] | 13 | 4.3
Psychiatric disorder
Insomnia | 15 | 0
The table includes a combination of grouped and ungrouped terms. Adverse reactions were graded based on CTCAE Version 4.0, with the exception of CRS, which was graded per ASTCT 2019 criteria.

Clinically relevant adverse reactions in < 10% of patients who received LUNSUMIO VELO included pruritus, skin exfoliation, herpes zoster infection, tremor, sepsis, cytomegalovirus (CMV) infection, ICANS, febrile neutropenia, capillary leak syndrome, tumor flare, and HLH .

Table 8 summarizes select laboratory abnormalities.

Table 8. Select Laboratory Abnormalities (≥ 20%) That Worsened from Baseline in Patients with Relapsed or Refractory FL Who Received LUNSUMIO VELO Subcutaneous Injection in GO29781
Laboratory Abnormality | LUNSUMIO VELO [The denominator used to calculate the rate varied from 85 to 94 based on the number of patients with a baseline value and at least one post-treatment value.]
Laboratory Abnormality | All Grades (%) | Grade 3 or 4 (%)
Hematology
Lymphocyte count decreased | 84 | 69
Hemoglobin decreased | 60 | 10
Neutrophils decreased | 50 | 26
Platelets decreased | 33 | 6.4
Chemistry
Phosphate decreased | 48 | 11
Alanine aminotransferase increased | 34 | 1.1
Gamma-glutamyl transferase increased | 31 | 1.1
Uric acid increased | 28 | 28
Aspartate aminotransferase increased | 28 | 2.1
Potassium decreased | 27 | 0
Magnesium decreased | 25 | 2.1

Clinically relevant laboratory abnormalities in < 20% of patients included glucose increased.

7 DRUG INTERACTIONS

Effect of LUNSUMIO VELO on CYP450 Substrates

LUNSUMIO VELO causes release of cytokines [see Clinical Pharmacology (12.2)] that may suppress activity of CYP450 enzymes, resulting in increased exposure of CYP450 substrates. Increased exposure of CYP450 substrates is more likely to occur after the first dose of LUNSUMIO VELO on Cycle 1 Day 1 and up to 14 days after the 45 mg dose on Cycle 1 Day 8 and during and after CRS [see Warnings and Precautions (5.1)]. Monitor for toxicity or concentrations of drugs that are CYP450 substrates where minimal concentration changes may lead to serious adverse reactions. Consult the concomitant CYP450 substrate drug prescribing information for recommended dosage modification.

8 USE IN SPECIFIC POPULATIONS

8.1 Pregnancy

Risk Summary

Based on the mechanism of action, LUNSUMIO VELO may cause fetal harm when administered to a pregnant woman [see Clinical Pharmacology (12.1)]. There are no available data on the use of LUNSUMIO VELO in pregnant women to evaluate for a drug-associated risk. No animal reproductive or developmental toxicity studies have been conducted with mosunetuzumab-axgb.

Mosunetuzumab-axgb causes T-cell activation and cytokine release; immune activation may compromise pregnancy maintenance. In addition, based on expression of CD20 on B-cells and the finding of B-cell depletion in non-pregnant animals, mosunetuzumab-axgb can cause B-cell lymphocytopenia in infants exposed to mosunetuzumab-axgb in-utero. Human immunoglobulin G (IgG) is known to cross the placenta; therefore, LUNSUMIO VELO has the potential to be transmitted from the mother to the developing fetus. Advise women of the potential risk to the fetus.

In the U.S. general population, the estimated background risk of major birth defects and miscarriage in clinically recognized pregnancies is 2% – 4% and 15% – 20%, respectively.

8.2 Lactation

Risk Summary

There is no information regarding the presence of mosunetuzumab-axgb in human milk, the effect on the breastfed child, or milk production. Because human IgG is present in human milk, and there is potential for mosunetuzumab-axgb absorption leading to B-cell depletion, advise women not to breastfeed during treatment with LUNSUMIO VELO and for 3 months after the last dose.

8.3 Females and Males of Reproductive Potential

LUNSUMIO VELO may cause fetal harm when administered to a pregnant woman [see Use in Specific Populations (8.1)].

Pregnancy Testing

Verify pregnancy status in females of reproductive potential prior to initiating LUNSUMIO VELO.

Contraception

Females

Advise females of reproductive potential to use effective contraception during treatment with LUNSUMIO VELO and for 3 months after the last dose.

8.4 Pediatric Use

The safety and efficacy of LUNSUMIO VELO have not been established in pediatric patients.

8.5 Geriatric Use

Among the 94 patients treated with LUNSUMIO VELO, 51% were 65 years of age or older. There is an insufficient number of patients 65 years of age or older to assess whether there are differences in safety or effectiveness by age group.

11 DESCRIPTION

Mosunetuzumab-axgb is a bispecific CD20-directed CD3 T-cell engager. It is a humanized monoclonal anti-CD20xCD3 T-cell-dependent bispecific antibody of the immunoglobulin G1 (IgG1) isotype. Mosunetuzumab-axgb is produced in Chinese Hamster Ovary (CHO) cells by recombinant DNA technology. The approximate molecular weight is 146 kDa.

LUNSUMIO VELO (mosunetuzumab-axgb) injection is a sterile, preservative-free, colorless to slightly brownish-yellow solution for subcutaneous use.

Each single-dose vial contains a 0.5 mL solution of mosunetuzumab-axgb (5 mg), acetic acid (0.2 mg), histidine (0.8 mg), methionine (0.7 mg), polysorbate 20 (0.3 mg), sucrose (41 mg), and Water for Injection, USP. The pH is 5.8.

Each single-dose vial contains a 1 mL solution of mosunetuzumab-axgb (45 mg), acetic acid (0.4 mg), histidine (1.6 mg), methionine (1.5 mg), polysorbate 20 (0.6 mg), sucrose (82.1 mg), and Water for Injection, USP. The pH is 5.8.

12 CLINICAL PHARMACOLOGY

12.1 Mechanism of Action

Mosunetuzumab-axgb is a T-cell engaging bispecific antibody that binds to the CD3 receptor expressed on the surface of T-cells and CD20 expressed on the surface of lymphoma cells and some healthy B-lineage cells.

In vitro, mosunetuzumab-axgb activated T-cells, caused the release of proinflammatory cytokines, and induced lysis of B-cells.

12.2 Pharmacodynamics

After subcutaneous administration of the recommended dosage of LUNSUMIO VELO, peripheral B-cell counts decreased to undetectable levels (< 5 cells/microliter) in most patients (94%) by Cycle 2 Day 1 and the depletion was sustained at later cycles including at Cycle 4 and Cycle 8.

LUNSUMIO VELO caused hypogammaglobulinemia (defined as IgG levels < 500 mg/dL). Among 49 patients with baseline IgG levels ≥ 500 mg/dL, 39% experienced a decrease in their IgG levels to < 500 mg/dL after receiving LUNSUMIO VELO.

Plasma concentrations of cytokines (IL-2, IL-6, IL-10, TNF-α and IFN-γ) were measured with subcutaneous administration of LUNSUMIO VELO, and transient elevation of cytokines were observed at doses of 1.6 mg and above. After administration of the recommended dosage of LUNSUMIO VELO, the highest elevation of cytokines was generally observed within 48 hours after the first dose on Cycle 1 Day 8 and generally returned to baseline prior to the third 45 mg full dose on Cycle 2 Day 1. The observed pattern of cytokine release appeared slower and reduced relative to intravenous administration.

12.3 Pharmacokinetics

Mosunetuzumab-axgb subcutaneously administered PK exposure increased proportionally over a dose range from 1.6 mg to 45 mg (0.04 to 1 times the recommended treatment dosage).

When comparing mosunetuzumab exposures following the recommended LUNSUMIO VELO subcutaneous dosing regimen to the recommended LUNSUMIO intravenous dosing regimen in patients with relapsed or refractory follicular lymphoma in Study GO29781 [see Clinical Studies (14)], the geometric mean ratios (GMRs) (90% CI) for observed Cycle 3 Ctrough was 1.39 (1.20 to 1.61) and AUC over 0-84 days was 1.06 (0.92 to 1.21). PK exposures for the recommended dosage of LUNSUMIO VELO via subcutaneous injection are summarized in Table 9 and Figure 1.

Table 9. Exposure Parameters of Mosunetuzumab-axgb Subcutaneous Injection
 | AUC (day∙µg/mL) [Values are geometric mean with geometric CV%.] | Cmax (µg/mL) | Ctrough (µg/mL)
Cycle 1 (0 – 21 days) | 36.7 (57.0) | 3.8 (53.9) | 3.5 (54.1)
Cycle 2 (21 – 42 days) | 82.3 (50.9) | 5.2 (50.3) | 2.5 (55.7)
Cycle 3 (42 – 63 days) | 72.9 (42.8) | 4.5 (44.0) | 2.4 (52.3)
Steady state [Steady state values are approximated at Cycle 4 (63 – 84 days).] | 72.8 (34.5) | 4.4 (36.7) | 2.4 (34.2)
All values reported are model-predicted exposure metrics.

Figure 1. Model-Predicted Mosunetuzumab-axgb Subcutaneous Injection Concentration Time Profile

Pharmacokinetic parameters (Table 10) were evaluated at the recommended dosage and are presented as geometric mean (CV%) unless otherwise specified.

Table 10. Mosunetuzumab-axgb Pharmacokinetic Parameters in Patients with Relapsed or Refractory Follicular Lymphoma
Parameter | LUNSUMIO VELO via Subcutaneous Infusion
Bioavailability | 89.8%
Tmax median (range), days [Steady-state] | 4.2 (2.5 – 7.1)
Volume of distributiona (L) | 5.5 (31%)
Half-lifea (days) | 17.0 (15%)
Systemic clearance (L/day) | 1.1 (63%) at baseline 0.58 (18%) at steady state
Tmax = time to peak concentration

Specific Populations

There were no clinically significant differences in the pharmacokinetics of mosunetuzumab-axgb based on age (18 to 96 years), sex, race (Asian and Non-Asian), ethnicity (Hispanic/Latino and not Hispanic/Latino), mild or moderate renal impairment (estimated creatinine clearance [CrCL] by Cockcroft-Gault formula: 30 to 89 mL/min), or mild hepatic impairment (total bilirubin less than or equal to upper limit of normal [ULN] with AST greater than ULN or total bilirubin greater than 1 to 1.5 times ULN with any AST).

The effects of severe renal impairment (CrCL 15 to 29 mL/min) or moderate to severe hepatic impairment (total bilirubin greater than 1.5 times ULN with any AST) on the pharmacokinetics of mosunetuzumab-axgb are unknown.

Drug Interaction Studies

No clinical studies evaluating the drug interaction potential of mosunetuzumab-axgb have been conducted.

12.6 Immunogenicity

The observed incidence of anti-drug antibodies is highly dependent on the sensitivity and specificity of the assay. Differences in assay methods preclude meaningful comparisons of the incidence of anti-drug antibodies in the study described below with the incidence of anti-drug antibodies in other studies, including those of mosunetuzumab-axgb.

During treatment in Study GO29781 (up to 12 months) [see Clinical Studies (14)], using an enzyme-linked immunosorbent assay (ELISA), no patients (N = 216) treated with LUNSUMIO VELO monotherapy developed anti-mosunetuzumab-axgb antibodies. Based on these data, the clinical relevance of anti-mosunetuzumab-axgb antibodies could not be assessed.

13 NONCLINICAL TOXICOLOGY

13.1 Carcinogenesis, Mutagenesis, Impairment of Fertility

No carcinogenicity or genotoxicity studies have been conducted with mosunetuzumab-axgb.

No dedicated studies have been conducted to evaluate the effects of mosunetuzumab-axgb on fertility. No adverse effects on either male or female reproductive organs were identified in a 26-week repeat dose chronic toxicity study in sexually mature cynomolgus monkeys.

14 CLINICAL STUDIES

The efficacy of LUNSUMIO VELO was evaluated in an open-label, multicenter, multi-cohort study (GO29781, NCT02500407) in patients with relapsed or refractory FL after at least two lines of systemic therapy, including an anti-CD20 monoclonal antibody and an alkylating agent. The study excluded patients with active infections, history of autoimmune disease, prior allogeneic transplant, or any history of central nervous system (CNS) lymphoma or CNS disorders.

Patients received 5 mg on Cycle 1 Day 1 and 45 mg on Cycle 1 Day 8, followed by 45 mg on Cycle 1 Day 15, then 45 mg via subcutaneous injection every 3 weeks in subsequent cycles. A treatment cycle was 21 days. LUNSUMIO VELO was administered for 8 cycles unless patients experienced progressive disease or unacceptable toxicity. After 8 cycles, patients with a complete response discontinued therapy; patients with a partial response or stable disease continued treatment up to 17 cycles, unless patients experienced progressive disease or unacceptable toxicity.

Among the 94 patients, the median age was 65 years (range: 35 to 84) with 49% being age > 65; 56% were male; 85% were White, 11% Asian, 2% Black, and 2% Hispanic or Latino. All had an Eastern Cooperative Oncology Group (ECOG) performance status of 0 or 1. The median number of prior lines of systemic therapy was 3 (range: 2 to 9), with 47% receiving 2 prior lines, 19% receiving 3 prior lines, and 34% receiving 4 or more prior lines.

Sixty-seven percent of patients had refractory disease to prior anti-CD20 monoclonal antibody therapy, 46% had refractory disease to both an anti-CD20 monoclonal antibody and alkylator, 20% had prior autologous stem cell transplant, 16% had prior rituximab plus lenalidomide, and 4% had prior CAR-T therapy. Twenty-five percent had bulky disease, and 44% had progression of disease within 24 months of first systemic therapy.

Efficacy was established on the basis of objective response rate (ORR) and duration of response (DOR) as assessed by an independent review facility using 2007 International Working Group criteria. Efficacy results are summarized in Table 11. The median follow-up for DOR was 16.0 months.

Table 11. Efficacy Results in Patients with Relapsed or Refractory FL Who Received LUNSUMIO VELO Subcutaneous Injection
Response | LUNSUMIO VELO N=94
Objective response rate, n (%) | 70 (75)
(95% CI) | (64, 83)
Complete response, n (%) | 55 (59)
(95% CI) | (48, 69)
Partial response, n (%) | 15 (16)
(95% CI) | (9, 25)
Duration of response [DOR is defined as time from first documented PR or CR to documented disease progression or death due to any cause.] , [Kaplan-Meier estimate.] | N = 70
Median DOR, months (95% CI) | 22.4 (16.8, 22.8)
Rate of continued response
At 12 months,% | 70
(95% CI) | (59, 81)
At 18 months, % | 60
(95% CI) | (46, 73)
DOR = duration of response; CI = confidence interval

The median time to first response was 2.8 months (range: 1.2 to 16.0).

16 HOW SUPPLIED/STORAGE AND HANDLING

LUNSUMIO VELO (mosunetuzumab-axgb) injection is a sterile, colorless to slightly brownish-yellow, preservative-free solution for subcutaneous injection supplied as follows:

- One 5 mg/0.5 mL single-dose vial in a carton (NDC 50242-177-01)
- One 45 mg/mL single-dose vial in a carton (NDC 50242-201-01).

STORAGE AND HANDLING

Store refrigerated at 2°C to 8°C (36°F to 46°F) in the original carton to protect from light.

Do not freeze. Do not shake.

17 PATIENT COUNSELING INFORMATION

Advise the patient to read the FDA-approved patient labeling (Medication Guide).

Cytokine Release Syndrome (CRS) – Discuss the signs and symptoms associated with CRS, including fever, chills, hypotension, tachycardia, hypoxia, and headache. Counsel patients to seek immediate medical attention should signs or symptoms of CRS occur at any time. Advise patients who experience symptoms that impair consciousness not to drive and refrain from operating heavy or potentially dangerous machinery until events resolve [see Warnings and Precautions (5.1)].

Neurologic Toxicity, including ICANS – Discuss the signs and symptoms associated with neurologic toxicity, including ICANS, headache, peripheral neuropathy, dizziness, or mental status changes. Advise patients to immediately contact their healthcare provider if they experience any signs or symptoms of neurologic toxicity. Advise patients who experience neurologic toxicity that impairs consciousness to refrain from driving or operating heavy or potentially dangerous machinery until neurologic toxicity resolves [see Warnings and Precautions (5.2)].

Infections – Discuss the signs or symptoms associated with infection [see Warnings and Precautions (5.3)].

Hemophagocytic Lymphohistiocytosis (HLH) – Discuss the signs and symptoms associated with HLH, including fever, coagulopathy, cytopenias, and splenomegaly [see Warnings and Precautions (5.4)].

Cytopenias – Discuss the signs and symptoms associated with cytopenias, including neutropenia and febrile neutropenia, anemia, and thrombocytopenia [see Warnings and Precautions (5.5)].

Tumor Flare – Inform patients of the potential risk of tumor flare reaction and to report any signs and symptoms associated with this event to their healthcare provider for evaluation [see Warnings and Precautions (5.6)].

Injection-Site Reactions – Inform patients that injection site reactions may occur and to report any severe reactions [See Adverse Reactions (6.1)].

Embryo-Fetal Toxicity – Advise pregnant women of the potential risk to a fetus. Advise females of reproductive potential to inform their healthcare provider if they are pregnant or become pregnant [see Use in Specific Populations (8.1)]. Advise females of reproductive potential to use effective contraception during treatment with LUNSUMIO VELO and for 3 months after the last dose [see Use in Specific Populations (8.3)].

Lactation – Advise women not to breastfeed during treatment with LUNSUMIO VELO and for 3 months after the last dose [see Use in Specific Populations (8.2)].

Manufactured by:
Genentech, Inc.
A Member of the Roche Group
1 DNA Way
South San Francisco, CA 94080-4990

LUNSUMIO VELO is a trademark of Genentech, Inc.
©2025 Genentech, Inc.

U.S. License No.: 1048

MEDICATION GUIDE
LUNSUMIO VELO™ (lun-SUM-mee-oh VEH-low)
(mosunetuzumab-axgb)
injection, for subcutaneous use

What is the most important information I should know about LUNSUMIO VELO?
LUNSUMIO VELO can cause Cytokine Release Syndrome (CRS), a serious side effect that is common during treatment with LUNSUMIO VELO, and can also be severe or life-threatening.
Get medical help right away if you develop any signs or symptoms of CRS at any time, including:

- fever of 100.4°F (38°C) or higher
- chills
- low blood pressure
- fast or irregular heartbeat
- tiredness or weakness
- difficulty breathing

- headache
- confusion
- feeling anxious
- dizziness or light-headedness
- nausea
- vomiting

Due to the risk of CRS, you will receive LUNSUMIO VELO on a "step-up dosing schedule".

- The step-up dosing schedule is when you receive smaller "step-up" doses before receiving higher doses of LUNSUMIO VELO during your first cycle of treatment.
- If your dose of LUNSUMIO VELO is delayed for any reason, you may need to repeat the "step-up dosing schedule."
- You may receive medicines to help reduce your risk of CRS before your dose.
- See "How will I receive LUNSUMIO VELO?" for more information about how you will receive LUNSUMIO VELO.

Your healthcare provider will check you for CRS during treatment with LUNSUMIO VELO and may treat you in a hospital if you develop signs and symptoms of CRS. Your healthcare provider may temporarily stop or completely stop your treatment with LUNSUMIO VELO if you have severe side effects.
See "What are the possible side effects of LUNSUMIO VELO?" for more information about side effects.

What is LUNSUMIO VELO?
LUNSUMIO VELO is a prescription medicine used to treat adults with follicular lymphoma whose cancer has come back or did not respond to previous treatment, and who have already received two or more treatments.
It is not known if LUNSUMIO VELO is safe and effective in children.

Before receiving LUNSUMIO VELO, tell your healthcare provider about all of your medical conditions, including if you:

- have an infection or have had an infection in the past which lasted a long time or keeps coming back.
- have or had Epstein-Barr Virus.
- are pregnant or plan to become pregnant. LUNSUMIO VELO may harm your unborn baby. Tell your healthcare provider right away if you become pregnant or think you may be pregnant during treatment with LUNSUMIO VELO.
  Females who are able to become pregnant:
  - your healthcare provider should do a pregnancy test before you start treatment with LUNSUMIO VELO.
  - use an effective method of birth control (contraception) during your treatment and for 3 months after the last dose of LUNSUMIO VELO.
- are breastfeeding or plan to breastfeed. It is not known if LUNSUMIO VELO passes into your breast milk. Do not breastfeed during treatment and for 3 months after the last dose of LUNSUMIO VELO.

Tell your healthcare provider about all the medicines you take, including prescription and over-the-counter medicines, vitamins, and herbal supplements.

How will I receive LUNSUMIO VELO?

- LUNSUMIO VELO will be given to you by your healthcare provider as an injection under your skin (subcutaneous) in your stomach area (abdomen) or thigh.
- After you complete the weekly "step-up dosing schedule" in Cycle 1, LUNSUMIO VELO is given every 21 days.
- After Cycle 1, your healthcare provider will decide if you need to continue to take other medicines to help reduce side effects from LUNSUMIO VELO during future cycles.
- Your healthcare provider will decide how many treatment cycles you will receive of LUNSUMIO VELO.

See "What is the most important information I should know about LUNSUMIO VELO?" for more information about how you will receive LUNSUMIO VELO.

What should I avoid while receiving LUNSUMIO VELO?
Do not drive, operate heavy machinery, or do other dangerous activities if you develop dizziness, confusion, tremors, sleepiness, or any other symptoms that impair consciousness until your signs and symptoms go away. These may be signs and symptoms of CRS or neurologic problems.
See "What is the most important information I should know about LUNSUMIO VELO?" and "What are the possible side effects of LUNSUMIO VELO?" for more information about signs and symptoms of CRS and neurologic problems.

What are the possible side effects of LUNSUMIO VELO?
LUNSUMIO VELO can cause serious side effects, including:
See "What is the most important information I should know about LUNSUMIO VELO?"

- Neurologic problems. LUNSUMIO VELO can cause serious and life-threatening neurologic problems. Your healthcare provider will check you for neurologic problems during treatment with LUNSUMIO VELO. Your healthcare provider may also refer you to a healthcare provider who specializes in neurologic problems. Tell your healthcare provider right away if you develop any signs or symptoms of neurologic problems during or after treatment with LUNSUMIO VELO, including:

- headache
- numbness and tingling of the arms, legs, hands, or feet
- dizziness
- confusion and disorientation
- difficulty paying attention or understanding things
- forgetting things or forgetting who or where you are
- trouble speaking, reading, or writing

- sleepiness or trouble sleeping
- tremors
- loss of consciousness
- seizures
- muscle problems or muscle weakness
- loss of balance or trouble walking
- tiredness

- Serious infections. LUNSUMIO VELO can cause serious infections that may lead to death. Your healthcare provider will check you for signs and symptoms of infection before and during treatment. Tell your healthcare provider right away if you develop any signs or symptoms of infection during treatment with LUNSUMIO VELO, including:

- fever of 100.4°F (38°C) or higher
- cough
- chest pain
- tiredness
- shortness of breath

- painful rash
- sore throat
- pain during urination
- feeling weak or generally unwell

- Hemophagocytic lymphohistiocytosis (HLH). LUNSUMIO VELO can cause overactivity of the immune system, a condition called hemophagocytic lymphohistiocytosis (HLH). HLH can be life-threatening and has led to death in people treated with LUNSUMIO VELO. Your healthcare provider will check you for HLH especially if your CRS lasts longer than expected. Signs and symptoms of HLH include:

- fever
- enlarged spleen
- easy bruising

- low blood cell counts
- liver problems

- Low blood cell counts. Low blood cell counts are common during treatment with LUNSUMIO VELO and can also be serious or severe. Your healthcare provider will check your blood cell counts during treatment with LUNSUMIO VELO. LUNSUMIO VELO can cause the following low blood cell counts:

- low white blood cell counts (lymphopenia and neutropenia). Low white blood cells can increase your risk for infection.
- low red blood cell counts (anemia). Low red blood cells can cause tiredness and shortness of breath.
- low platelet counts (thrombocytopenia). Low platelet counts can cause bruising or bleeding problems.

- Growth in your tumor or worsening of tumor related problems (tumor flare). LUNSUMIO VELO can cause serious or severe worsening of your tumor. Tell your healthcare provider if you develop any of these signs or symptoms of tumor flare during your treatment with LUNSUMIO VELO:

- chest pain
- cough
- trouble breathing

- tender or swollen lymph nodes
- pain or swelling at the site of the tumor

Your healthcare provider may temporarily stop or permanently stop treatment with LUNSUMIO VELO if you develop severe side effects.
The most common side effects of LUNSUMIO VELO include:

- injection site reactions
- tiredness
- rash
- CRS

- COVID-19
- muscle and joint pain
- diarrhea

The most common severe abnormal blood test results with LUNSUMIO VELO include: decreased white blood cell counts and increased uric acid levels.
These are not all of the possible side effects of LUNSUMIO VELO.
Call your doctor for medical advice about side effects. You may report side effects to FDA at 1-800-FDA-1088.

General information about the safe and effective use of LUNSUMIO VELO.
Medicines are sometimes prescribed for purposes other than those listed in a Medication Guide. You can ask your pharmacist or healthcare provider for information about LUNSUMIO VELO that is written for health professionals.

What are the ingredients in LUNSUMIO VELO?
Active ingredient: mosunetuzumab-axgb
Inactive ingredients: acetic acid, histidine, methionine, polysorbate 20, sucrose, and Water for Injection.
Manufactured by: Genentech, Inc., A Member of the Roche Group, 1 DNA Way, South San Francisco, CA 94080-4990
U.S. License No.: 1048
LUNSUMIO VELO is a trademark of Genentech, Inc.
For more information, call 1-844-832-3687 or go to www.LUNSUMIO.com.

This Medication Guide has been approved by the U.S. Food and Drug Administration.

Issued: Dec 2025

PRINCIPAL DISPLAY PANEL - 5 mg/0.5 mL Vial Carton

NDC 50242-177-01

Lunsumio Velo™

(mosunetuzumab-axgb)
Injection

5 mg/0.5 mL

For Subcutaneous Use Only.

Single-Dose Vial.
Discard Unused Portion.

ATTENTION: Dispense the enclosed
Medication Guide to each patient.

1 vial

Rx only
Genentech
11027680

PRINCIPAL DISPLAY PANEL - 45 mg/mL Vial Carton

NDC 50242-201-01

Lunsumio Velo™

(mosunetuzumab-axgb)
Injection

45 mg/mL

For Subcutaneous Use Only.

Single-Dose Vial.
Discard Unused Portion.

ATTENTION: Dispense the enclosed
Medication Guide to each patient.

1 vial

Rx only
Genentech
11027612